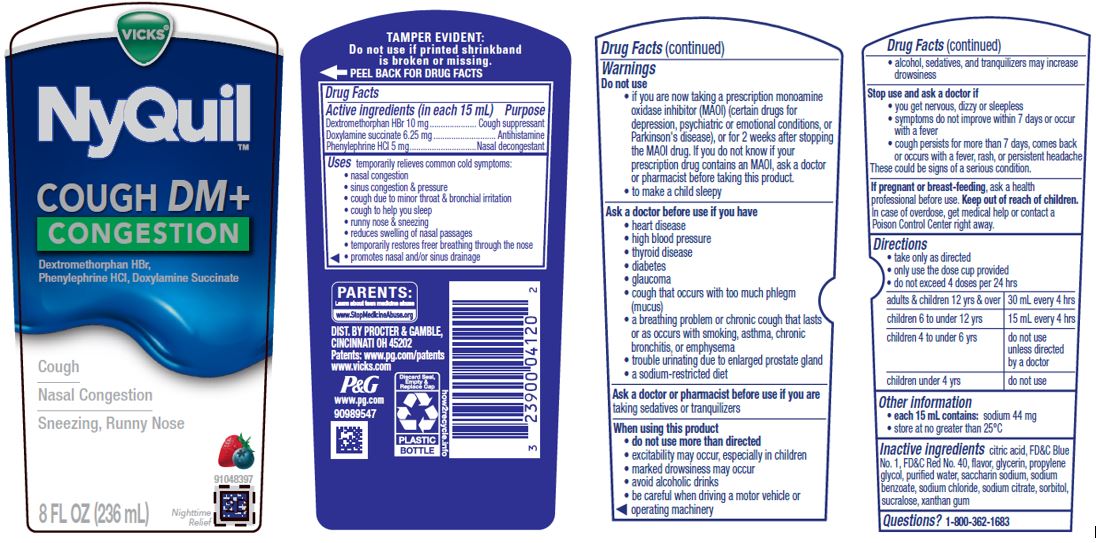 DRUG LABEL: Vicks NyQuil
NDC: 69423-999 | Form: LIQUID
Manufacturer: The Procter & Gamble Manufacturing Company
Category: otc | Type: HUMAN OTC DRUG LABEL
Date: 20251002

ACTIVE INGREDIENTS: PHENYLEPHRINE HYDROCHLORIDE 5 mg/15 mL; DEXTROMETHORPHAN HYDROBROMIDE 10 mg/15 mL; DOXYLAMINE SUCCINATE 6.25 mg/15 mL
INACTIVE INGREDIENTS: SUCRALOSE; XANTHAN GUM; GLYCERIN; CITRIC ACID MONOHYDRATE; FD&C BLUE NO. 1; FD&C RED NO. 40; SODIUM CHLORIDE; SODIUM BENZOATE; PROPYLENE GLYCOL; WATER; SACCHARIN SODIUM; SODIUM CITRATE; SORBITOL

VICKS® NyQuil™
COUGH DM + CONGESTION

Drug Facts

Active ingredients (in each 15 mL)

Dextromethorphan HBr 10 mg

Doxylamine succinate 6.25 mg

Phenylephrine HCl 5 mg

Purpose

Cough suppressant

Antihistamine

Nasal decongestant

Uses

temporarily relieves cold symptoms:

• nasal congestion
• sinus congestion & pressure
• cough due to minor throat & bronchial irritation
• cough to help you sleep
• runny nose & sneezing
• reduces swelling of nasal passages
• temporarily restores freer breathing through the nose
• promotes nasal and/or sinus drainage

Warnings

Do not use

- if you are now taking a prescription monoamine oxidase inhibitor (MAOI) (certain drugs for depression, psychiatric or emotional conditions, or Parkinson's disease), or for 2 weeks after stopping the MAOI drug. If you do not know if your prescription drug contains an MAOI, ask a doctor or pharmacist before taking this product.
- to make a child sleepy

Ask a doctor before use if you have

• heart disease
• high blood pressure
• thyroid disease
• diabetes
• glaucoma
• cough that occurs with too much phlegm (mucus)
• a breathing problem or chronic cough that lasts or as occurs with smoking, asthma, chronic bronchitis, or emphysema
• trouble urinating due to enlarged prostate gland
• a sodium-restricted diet

Ask a doctor or pharmacist before use if you are taking sedatives or tranquilizers.

When using this product

- do not use more than directed
- excitability may occur, especially in children
- marked drowsiness may occur
- avoid alcoholic drinks
- be careful when driving a motor vehicle or operating machinery
- alcohol, sedatives, and tranquilizers may increase drowsiness

Stop use and ask a doctor if

- you get nervous, dizzy or sleepless
- symptoms do not improve within 7 days or occur with a fever
- cough persists for more than 7 days, comes back or occurs with a fever, rash, or persistent headache.

These could be signs of a serious condition.

PREGNANCY OR BREAST FEEDING

If pregnant or breast-feeding, ask a health professional before use.

Keep out of reach of children. In case of overdose, get medical help or contact a Poison Control Center right away.

Directions

- take only as directed
- only use dose cup provided
- do not exceed 4 doses per 24 hrs

adults & children 12 yrs & over | 30 mL every 4 hrs
children 6 to under 12 yrs | 15 mL every 4 hrs
children 4 to under 6 yrs | not use unless directed by a doctor
children under 4 yrs | do not use

Other information

- each 15 mL dose cup contains: sodium 44 mg
- store at no greater than 25°C

Inactive ingredients

citric acid, FD&C Blue No. 1, FD&C Red No. 40, flavor, glycerin, propylene glycol, purified water, saccharin sodium, sodium benzoate, sodium chloride, sodium citrate, sorbitol, sucralose, xanthan gum

Questions?

1-800-362-1683

TAMPER EVIDENT: Do not use if printed shrinkband is broken or missing.

DIST. BY PROCTER & GAMBLE,
CINCINNATI OH 45202

PRINCIPAL DISPLAY PANEL - 236 ml Bottle Label

VICKS®

NyQuil™

COUGH DM + CONGESTION

Dextromethorphan HBr, Phenylephrine HCl, Doxylamine Succinate

- Cough
- Nasal Congestion
- Sneezing, Runny Nose

8 FL OZ (236 ml)

Nighttime Relief